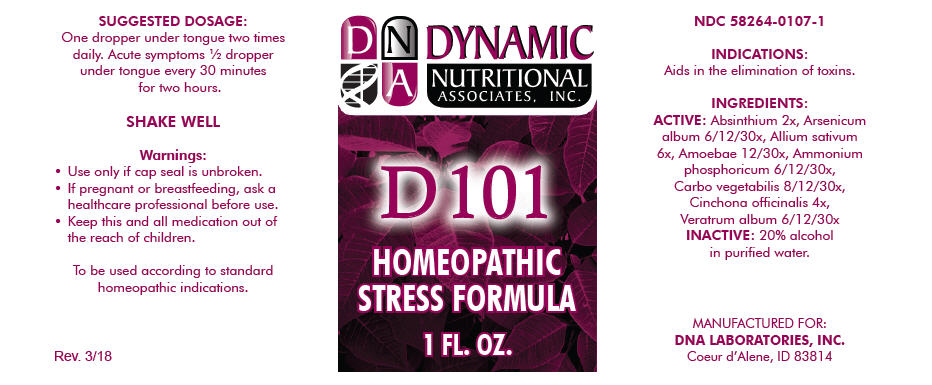 DRUG LABEL: D-101
NDC: 58264-0107 | Form: SOLUTION
Manufacturer: DNA Labs, Inc.
Category: homeopathic | Type: HUMAN OTC DRUG LABEL
Date: 20250113

ACTIVE INGREDIENTS: WORMWOOD 2 [hp_X]/1 mL; ARSENIC TRIOXIDE 6 [hp_X]/1 mL; GARLIC 6 [hp_X]/1 mL; AMOEBA PROTEUS 12 [hp_X]/1 mL; AMMONIUM PHOSPHATE, DIBASIC 6 [hp_X]/1 mL; ACTIVATED CHARCOAL 8 [hp_X]/1 mL; CINCHONA OFFICINALIS BARK 4 [hp_X]/1 mL; VERATRUM ALBUM ROOT 6 [hp_X]/1 mL
INACTIVE INGREDIENTS: ALCOHOL; WATER

D-101

NDC 58264-0107-1

INDICATIONS

PURPOSE

Aids in the elimination of toxins.

INGREDIENTS

ACTIVE

Absinthium 2x, Arsenicum album 6/12/30x, Allium sativum 6x, Amoebae 12/30x, Ammonium phosphoricum 6/12/30x, Carbo vegetabilis 8/12/30x, Cinchona officinalis 4x, Veratrum album 6/12/30x

INACTIVE

20% alcohol in purified water.

SUGGESTED DOSAGE

One dropper under tongue two times daily. Acute symptoms ½ dropper under tongue every 30 minutes for two hours.

STORAGE AND HANDLING

SHAKE WELL

Warnings

- Use only if cap seal is unbroken.

PREGNANCY OR BREAST FEEDING

- If pregnant or breastfeeding, ask a healthcare professional before use.

KEEP OUT OF REACH OF CHILDREN

- Keep this and all medication out of the reach of children.

To be used according to standard homeopathic indications.

PRINCIPAL DISPLAY PANEL - 1 FL. OZ. Bottle Label

DYNAMIC
NUTRITIONAL
ASSOCIATES, INC.

D 101

HOMEOPATHIC
STRESS FORMULA

1 FL. OZ.